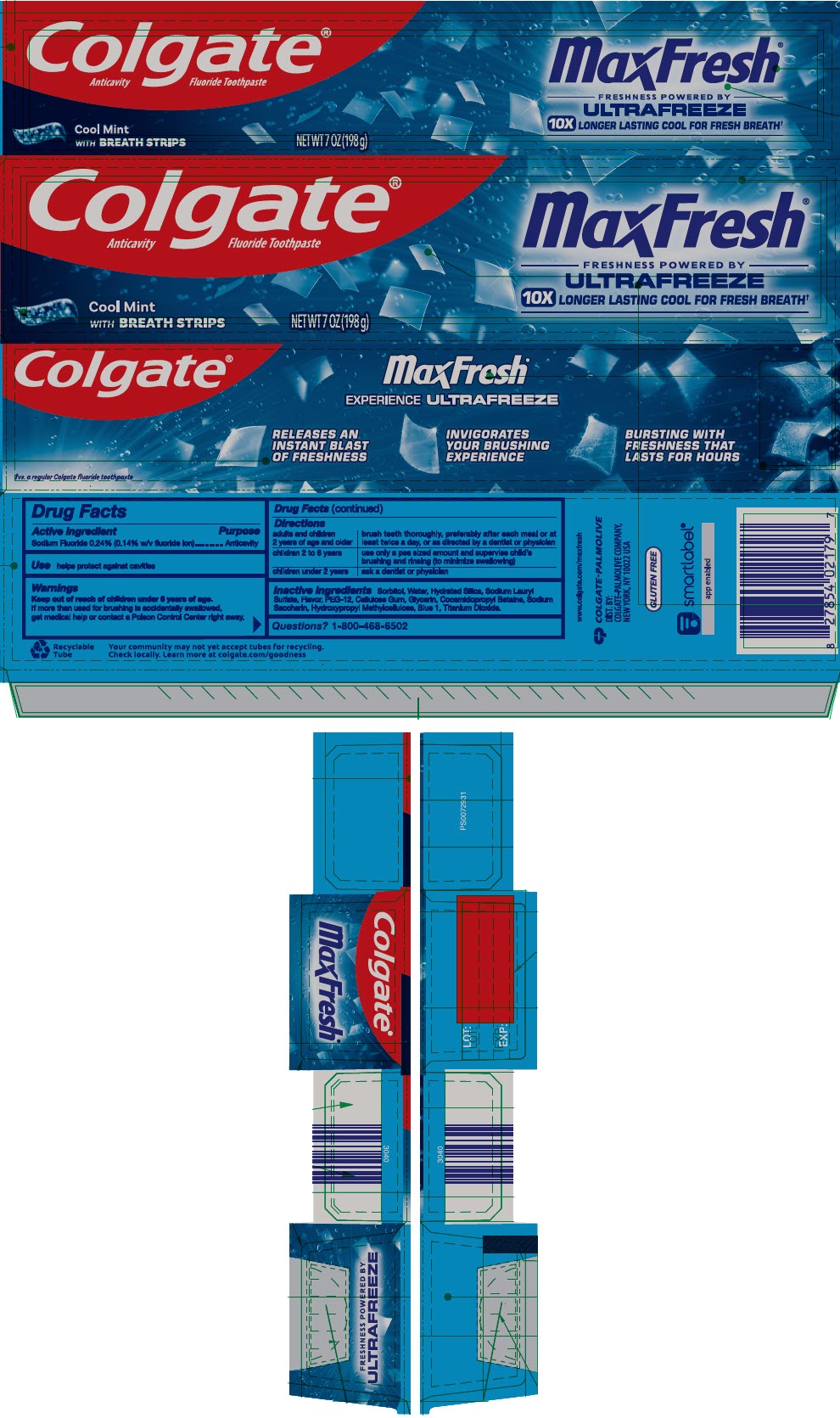 DRUG LABEL: Colgate MaxFresh Cool Mint
NDC: 35000-211 | Form: GEL, DENTIFRICE
Manufacturer: COLGATE PALMOLIVE COMPANY
Category: otc | Type: HUMAN OTC DRUG LABEL
Date: 20251015

ACTIVE INGREDIENTS: SODIUM FLUORIDE 1.1 mg/1 g
INACTIVE INGREDIENTS: SORBITOL; WATER; HYDRATED SILICA; SODIUM LAURYL SULFATE; POLYETHYLENE GLYCOL 600; CARBOXYMETHYLCELLULOSE SODIUM, UNSPECIFIED; GLYCERIN; COCAMIDOPROPYL BETAINE; SACCHARIN SODIUM; HYPROMELLOSE, UNSPECIFIED; FD&C BLUE NO. 1; TITANIUM DIOXIDE

Colgate® MaxFresh® Cool Mint

Drug Facts

Active ingredient

Sodium Fluoride 0.24% (0.14% w/v fluoride ion)

Purpose

Anticavity

Use

helps protect against cavities

Warnings

Keep out of reach of children under 6 years of age.

If more than used for brushing is accidentally swallowed, get medical help or contact a Poison Control Center right away.

Directions

adults and children 2 years of age and older | brush teeth thoroughly, preferably after each meal or at least twice a day, or as directed by a dentist or physician
children 2 to 6 years | use only a pea sized amount and supervise child's brushing and rinsing (to minimize swallowing)
children under 2 years | ask a dentist or physician

Inactive ingredients

Sorbitol, Water, Hydrated Silica, Sodium Lauryl Sulfate, Flavor, PEG-12, Cellulose Gum, Glycerin, Cocamidopropyl Betaine, Sodium Saccharin, Hydroxypropyl Methylcellulose, Blue 1, Titanium Dioxide.

Questions?

1-800-468-6502

DIST. BY:
COLGATE-PALMOLIVE COMPANY,
NEW YORK, NY 10022 USA

PRINCIPAL DISPLAY PANEL - 198 g Tube Carton

Colgate®
Anticavity Fluoride Toothpaste

MaxFresh®

FRESHNESS POWERED BY
ULTRA FREEZE

10X LONGER LASTING COOL FOR FRESH BREATH†

Cool Mint
with BREATH STRIPS

NET WT 7 OZ (198 g)